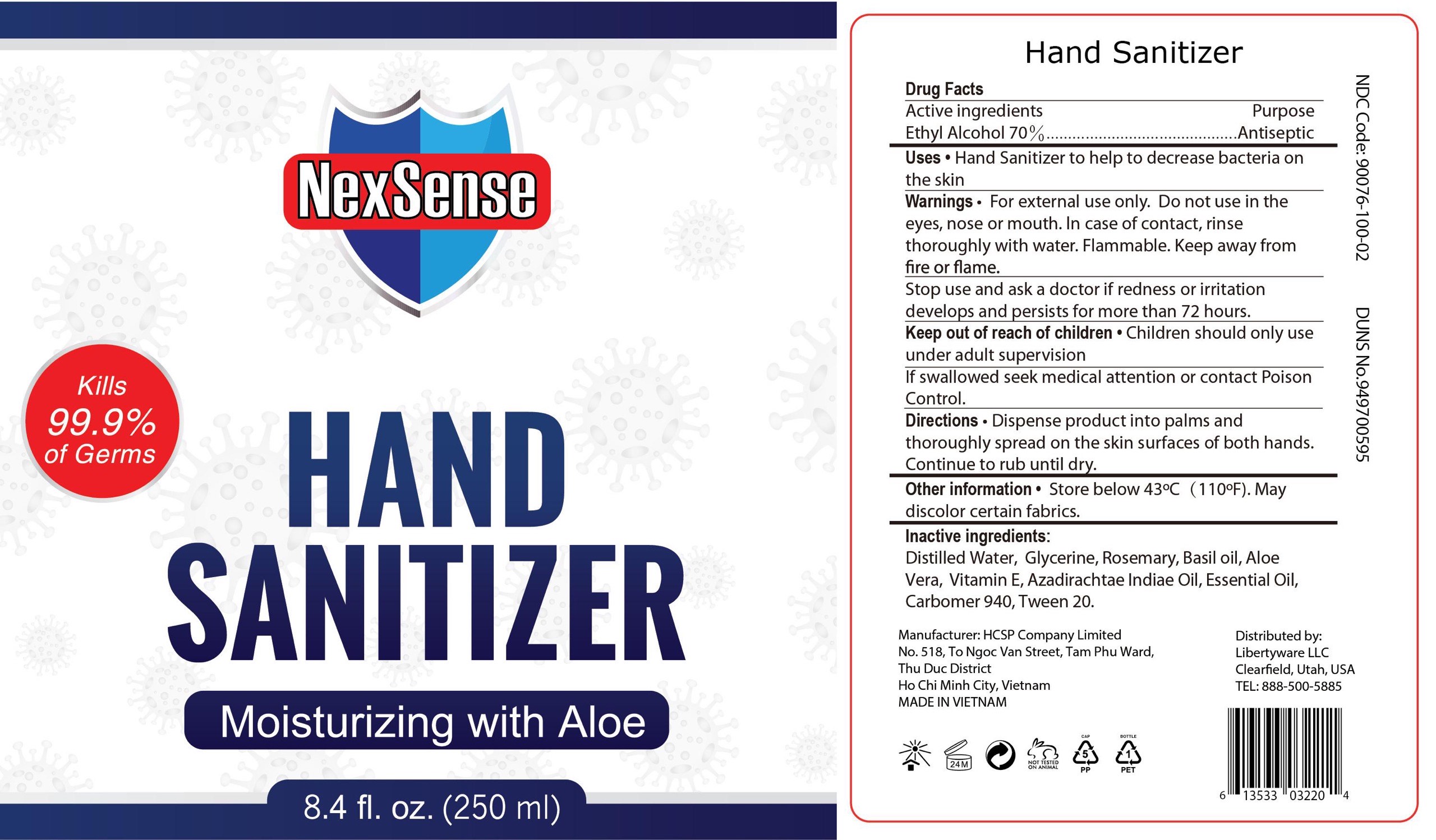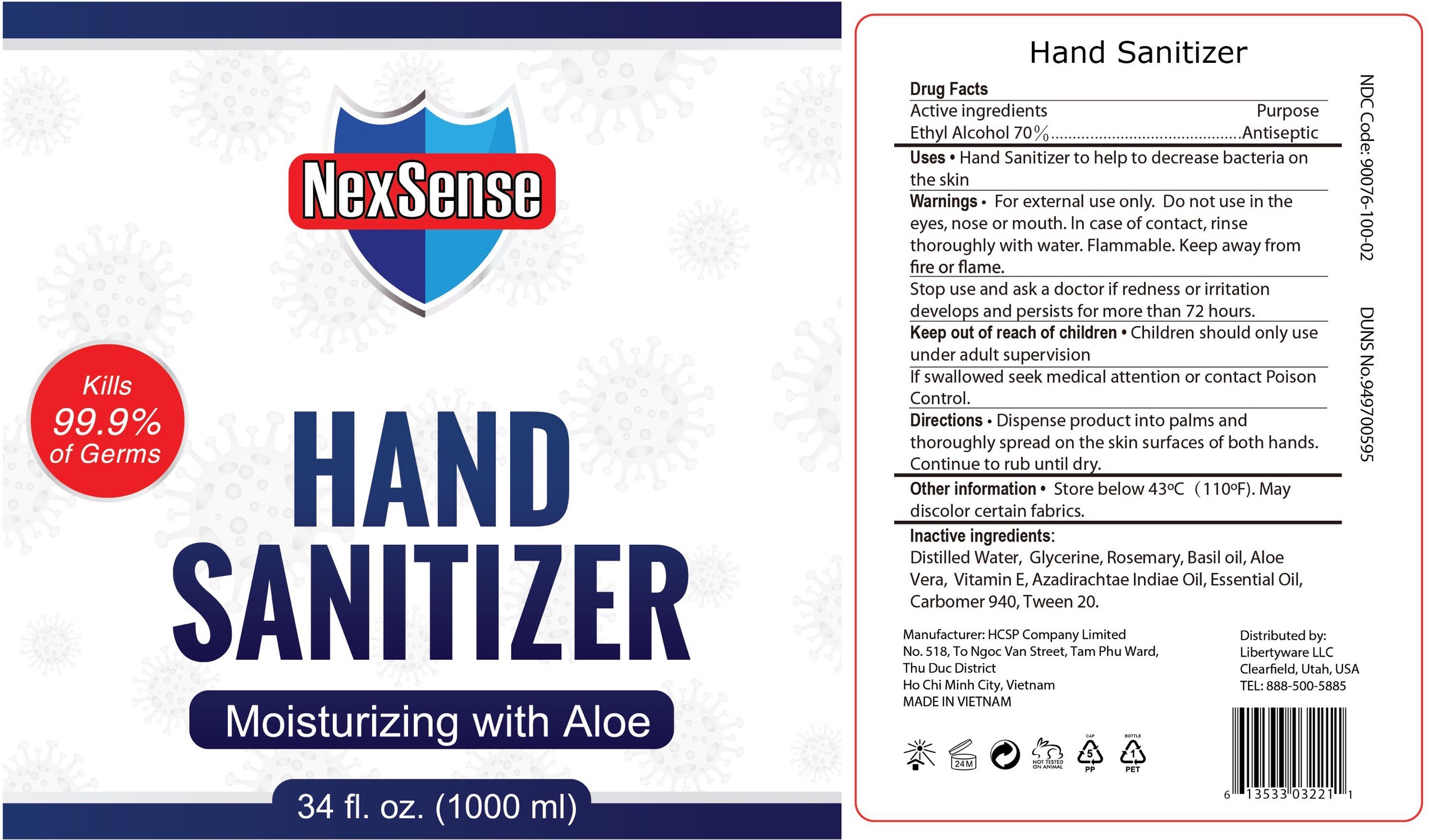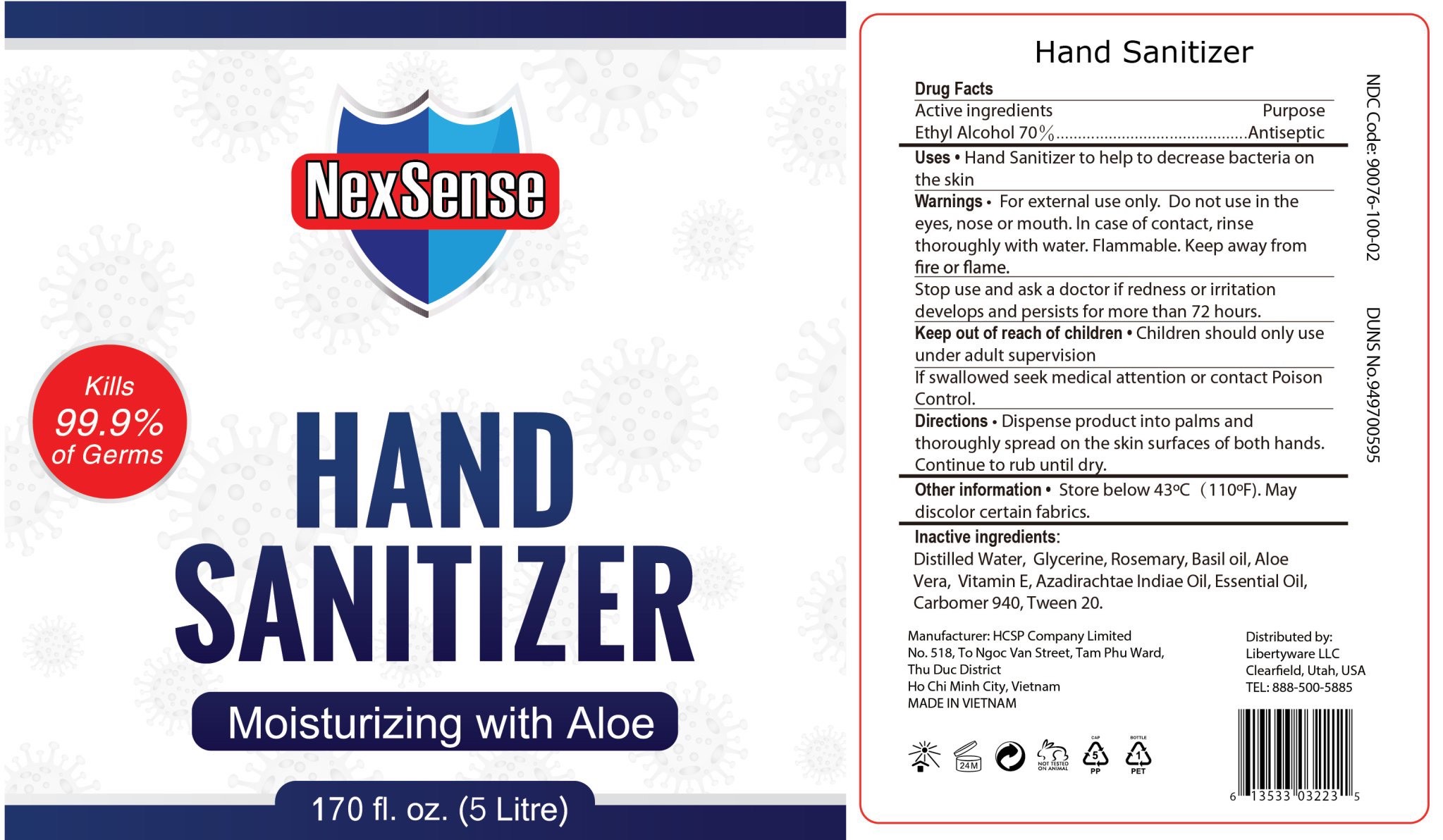 DRUG LABEL: Hand Sanitizer
NDC: 90076-100 | Form: GEL
Manufacturer: LibertyWare LLC
Category: otc | Type: HUMAN OTC DRUG LABEL
Date: 20201015

ACTIVE INGREDIENTS: ALCOHOL 70 mL/100 mL
INACTIVE INGREDIENTS: ALOE VERA LEAF 1 mL/100 mL; GLYCERIN 1.45 mL/100 mL; ROSEMARY 1.45 mL/100 mL; WATER 22.5 mL/100 mL; BASIL OIL 1.45 mL/100 mL; .ALPHA.-TOCOPHEROL 0.6 mL/100 mL; AZADIRACHTA INDICA SEED OIL 0.5 mL/100 mL; CARBOMER 940 0.4 mL/100 mL; POLYSORBATE 20 0.1 mL/100 mL

Active Ingredient(s)

Alcohol 70% v/v. Purpose: Antiseptic

Purpose

Antiseptic, Hand Sanitizer

Use

for handwashing to decrease bacteria on the skin.

Recommended for repeated use

Warnings

For external use only. Flammable. Keep away from heat or flame

Do not use

- in the eyes. In case of contact rinse eyes thoroughly with water.

WHEN USING

In case of contact with eyes, rinse eyes thoroughly with water.
Stop use and ask a doctor if irritation and redness develop and persist for more than 72 hours.

Keep out of reach of children. If swallowed, get medical help or contact a Poison Control Center right away.

Stop use and ask a doctor if irritation or rash occurs. These may be signs of a serious condition.

Keep out of reach of children. If swallowed, get medical help or contact a Poison Control Center right away.

Directions

- Apply products to hands
- Briskly rub hands together until dry
- Supervise children under 6 years in the use of this product

Other information

- Store below 100F (43C)
- May discolor certain fabrics

Inactive ingredients

distilled water, glycerin, rosemary, basil oil, aloe vera, vitamin e, azadirachtae indicae oil, essential oil, carbomer 940, tween 20

RECENT MAJOR CHANGES

Use: Change from template to label description

Direction: Change from template to label description

Package Label - Principal Display Panel

250 mL NDC: 90076-100-01

1000 mL NDC: 90076-100-02

5L NDC: 90076-100-03